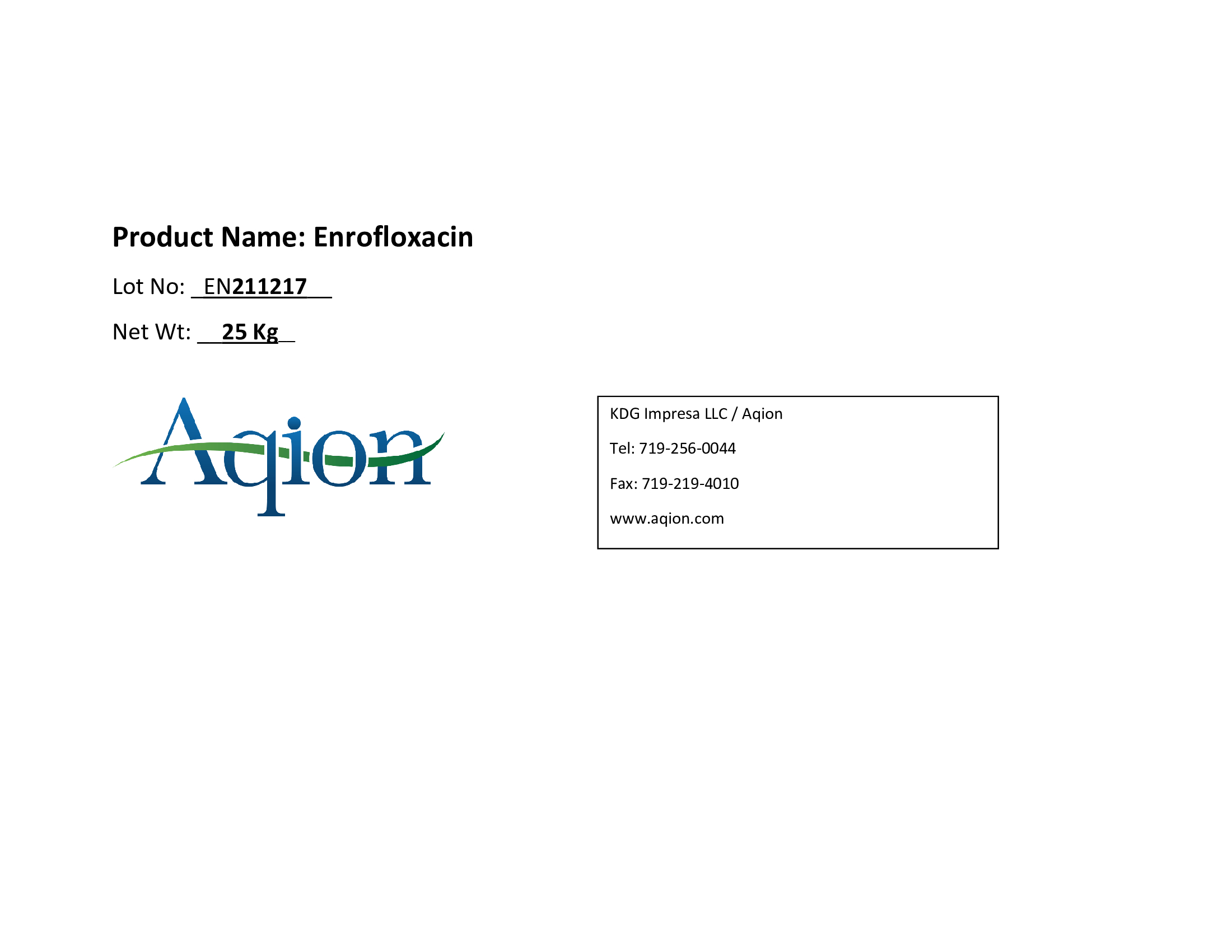 DRUG LABEL: Enrofloxacin
NDC: 43457-649 | Form: POWDER
Manufacturer: KDG Impresa LLC, Aqion
Category: other | Type: BULK INGREDIENT - ANIMAL DRUG
Date: 20231019

ACTIVE INGREDIENTS: Enrofloxacin 1 kg/1 kg

Enrofloxacin